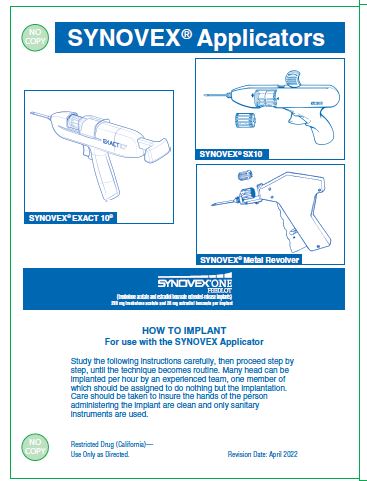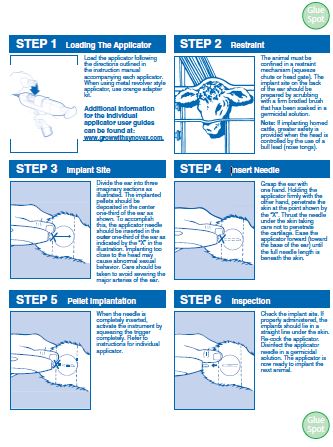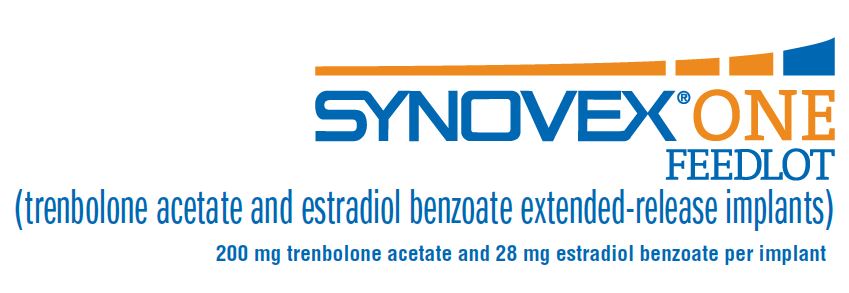 DRUG LABEL: Synovex One
NDC: 54771-2010 | Form: IMPLANT
Manufacturer: Zoetis Inc.
Category: animal | Type: OTC ANIMAL DRUG LABEL
Date: 20220809

ACTIVE INGREDIENTS: trenbolone acetate 200 mg/1 1; estradiol benzoate 28 mg/1 1

SYNOVEX® ONE FEEDLOT

SYNOVEX® ONE FEEDLOT
(trenbolone acetate and estradiol benzoate extended-release implants)
200 mg trenbolone acetate and 28 mg estradiol benzoate per implant

SUBCUTANEOUS IMPLANTS FOR STEERS AND HEIFERS FED IN CONFINEMENT FOR SLAUGHTER

DESCRIPTION

SYNOVEX® ONE Feedlot (trenbolone acetate and estradiol benzoate extended-release implants) is a growth promoting implant containing 200 mg of trenbolone acetate and 28 mg of estradiol benzoate per implant with a porous polymer film coating that extends the pay-out period of the final formulation up to 200 days. Each implant consists of 8 pellets. Ten implants are provided in each cartridge.
NOTE: Administration of a single SYNOVEX® ONE Feedlot implant or its use in a reimplantation program with a SYNOVEX Choice® implant may result in decreased marbling scores when compared to non-implanted steers and heifers.

WITHDRAWAL PERIODS AND RESIDUE WARNINGS

No withdrawal period is required when used according to labeling.
Do not use in beef calves less than 2 months of age, dairy calves, and veal calves. A withdrawal period has not been established for this product in pre-ruminating calves.
Do not use in dairy cows or in animals intended for subsequent breeding. Use in these cattle may cause drug residues in milk and/or in calves born to these cows.
Implant pellets subcutaneously in ear only. Any other location is a violation of Federal law. Do not attempt salvage of implanted site for human or animal food.

USER SAFETY WARNINGS

Not for use in humans. Keep out of reach of children.

ANIMAL SAFETY WARNING

Bulling has occasionally been reported in implanted steers and heifers. Vaginal and rectal prolapse, udder development, ventral edema and elevated tailheads have occasionally been reported in heifers administered SYNOVEX® ONE Feedlot implants.

DIRECTIONS

Administer one SYNOVEX® ONE Feedlot implant (eight pellets), containing 200 mg trenbolone acetate and 28 mg estradiol benzoate, to each steer or heifer by subcutaneous implantation in the middle-third of the ear. If using in a reimplantation program, reimplant steers or heifers with a SYNOVEX® ONE Feedlot implant 60 to 120 days after administering a SYNOVEX Choice® implant.
Use only a SYNOVEX applicator. Approved implantation technique is fully described in the fold-out carton section. Never sacrifice careful, clean technique for speed of implantation.

STORAGE

Store unopened product at controlled room temperature 20°-25°C (68°-77°F) with excursions between 15°-30°C (59°-86°F). Avoid excessive heat and humidity. Use product before the expiration date on the label.
Once the pouch is opened, unused product may be stored in the end-folded pouch (away from light) for up to six months under refrigerated conditions 2°-8°C (36°-47°F) or at room temperature 20°-25°C (68°-77°F) with excursions between 15°-30°C (59°-86°F) for up to one month.

DISPOSAL

SYNOVEX® ONE Feedlot waste materials should be disposed of according to prescribed Federal, State, and Local guidelines.

INDICATIONS FOR USE

•For increased rate of weight gain and improved feed efficiency for up to200 days in growing beef steers and heifers fed in confinement for slaughter.
•For increased rate of weight gain for up to 200 days in growing beef steersand heifers fed in confinement for slaughter in a reimplantation programwhere SYNOVEX Choice® is the first implant and a SYNOVEX® ONEFeedlot implant is administered 60 to 120 days later.
•Other than as described on the labeling, this implant is not approved forrepeated implantation (reimplantation) with any other cattle ear implant ingrowing beef steers and heifers fed in confinement for slaughter as safetyand effectiveness have not been evaluated.
Do not use in beef calves less than 2 months of age, dairy calves, and veal calves because effectiveness and safety have not been established.
Do not use in animals intended for subsequent breeding, or in dairy cows.

QUESTIONS/COMMENTS?

For a copy of the Safety Data Sheet or to report side effects, contact Zoetis Inc. at 1-888-963-8471. For additional informationabout reporting side effects for animaldrugs, contact FDA at 1-888-FDA-VETS orhttp://www.fda.gov/reportanimalae.

SYNOVEX Choice® (trenbolone acetate and estradiol benzoate implants) is owned by Zoetis.
Manufactured By A Non-Sterilizing Process
Restricted Drug (California)—Use Only As Directed.

IMPORTANT

Read ALL sides of carton

Approved by FDA under NADA # 141-348
zoetis
Distributed by:
Zoetis Inc.
Kalamazoo, MI 49007

Revision Date: April 2022
40037684